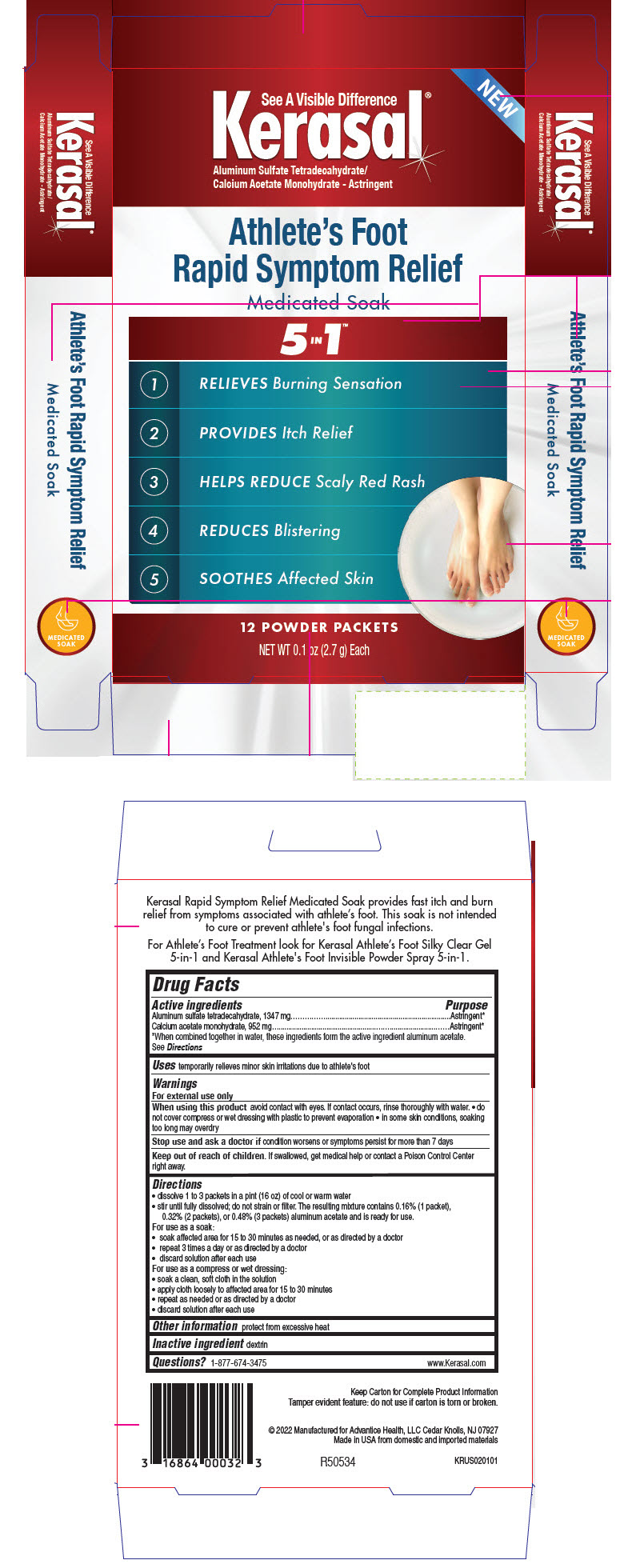 DRUG LABEL: Kerasal Athletes Foot Rapid Symptom Relief
NDC: 16864-140 | Form: POWDER, FOR SOLUTION
Manufacturer: Advantice Health, LLC.
Category: otc | Type: HUMAN OTC DRUG LABEL
Date: 20260126

ACTIVE INGREDIENTS: ALUMINUM SULFATE TETRADECAHYDRATE 1347 mg/1 1; CALCIUM ACETATE MONOHYDRATE 952 mg/1 1
INACTIVE INGREDIENTS: ICODEXTRIN

Kerasal®Athlete's Foot Rapid Symptom Relief
Medicated Soak

Drug Facts

ACTIVE INGREDIENT

Active ingredients | Purpose
Aluminum sulfate tetradecahydrate, 1347 mg | Astringent [When combined together in water, these ingredients form the active ingredient aluminum acetate.]
Calcium acetate monohydrate, 952 mg | Astringent

See Directions

Uses

temporarily relieves minor skin irritations due to athlete's foot

Warnings

For external use only

WHEN USING

When using this productavoid contact with eyes. If contact occurs, rinse thoroughly with water.

- do not cover compress or wet dressing with plastic to prevent evaporation
- in some skin conditions, soaking too long may overdry

Stop use and ask a doctor ifcondition worsens or symptoms persist for more than 7 days

Keep out of reach of children.If swallowed, get medical help or contact a Poison Control Center right away.

Directions

- dissolve 1 to 3 packets in a pint (16 oz) of cool or warm water
- stir until fully dissolved; do not strain or filter. The resulting mixture contains 0.16% (1 packet), 0.32% (2 packets), or 0.48% (3 packets) aluminum acetate and is ready for use.

For use as a soak:

- soak affected area for 15 to 30 minutes as needed, or as directed by a doctor
- repeat 3 times a day or as directed by a doctor
- discard solution after each use

For use as a compress or wet dressing:

- soak a clean, soft cloth in the solution
- apply cloth loosely to affected area for 15 to 30 minutes
- repeat as needed or as directed by a doctor
- discard solution after each use

Other information

protect from excessive heat

Inactive ingredient

dextrin

Questions?

1-877-674-3475

www.Kerasal.com

PRINCIPAL DISPLAY PANEL - 12 Packet Box

See A Visible Difference
Kerasal®
Aluminum Sulfate Tetradecahydrate/
Calcium Acetate Monohydrate - Astringent

NEW

Athlete's Foot
Rapid Symptom Relief
Medicated Soak

5 IN 1™

- RELIEVES Burning Sensation
- PROVIDES Itch Relief
- HELPS REDUCE Scaly Red Rash
- REDUCES Blistering
- SOOTHES Affected Skin

12 POWDER PACKETS

NET WT 0.1 oz (2.7 g) Each